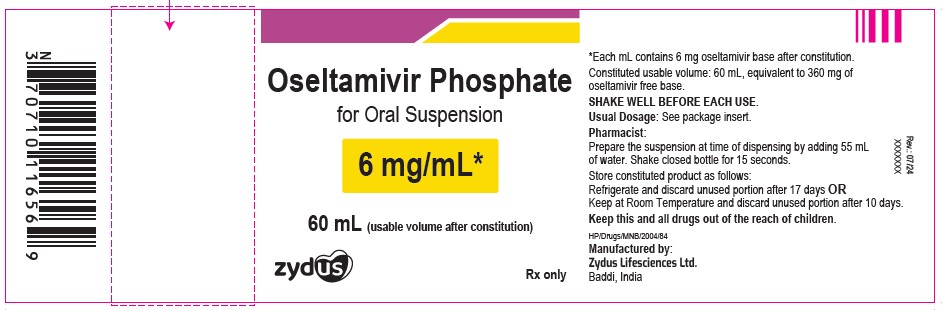 DRUG LABEL: Oseltamivir Phosphate
NDC: 70771-1598 | Form: SUSPENSION
Manufacturer: Zydus Lifesciences Limited
Category: prescription | Type: HUMAN PRESCRIPTION DRUG LABEL
Date: 20241209

ACTIVE INGREDIENTS: OSELTAMIVIR PHOSPHATE 6 mg/1 mL
INACTIVE INGREDIENTS: MONOSODIUM CITRATE; SACCHARIN SODIUM; SODIUM BENZOATE; SORBITOL; TITANIUM DIOXIDE; WATER; XANTHAN GUM

Oseltamivir Phosphate for Oral Suspension

PACKAGE LABEL.PRINCIPAL DISPLAY PANEL

NDC 70771-1598-6

Oseltamivir Phosphate for Oral Suspension

6 mg/mL *

60 mL (usable volume after constitution)